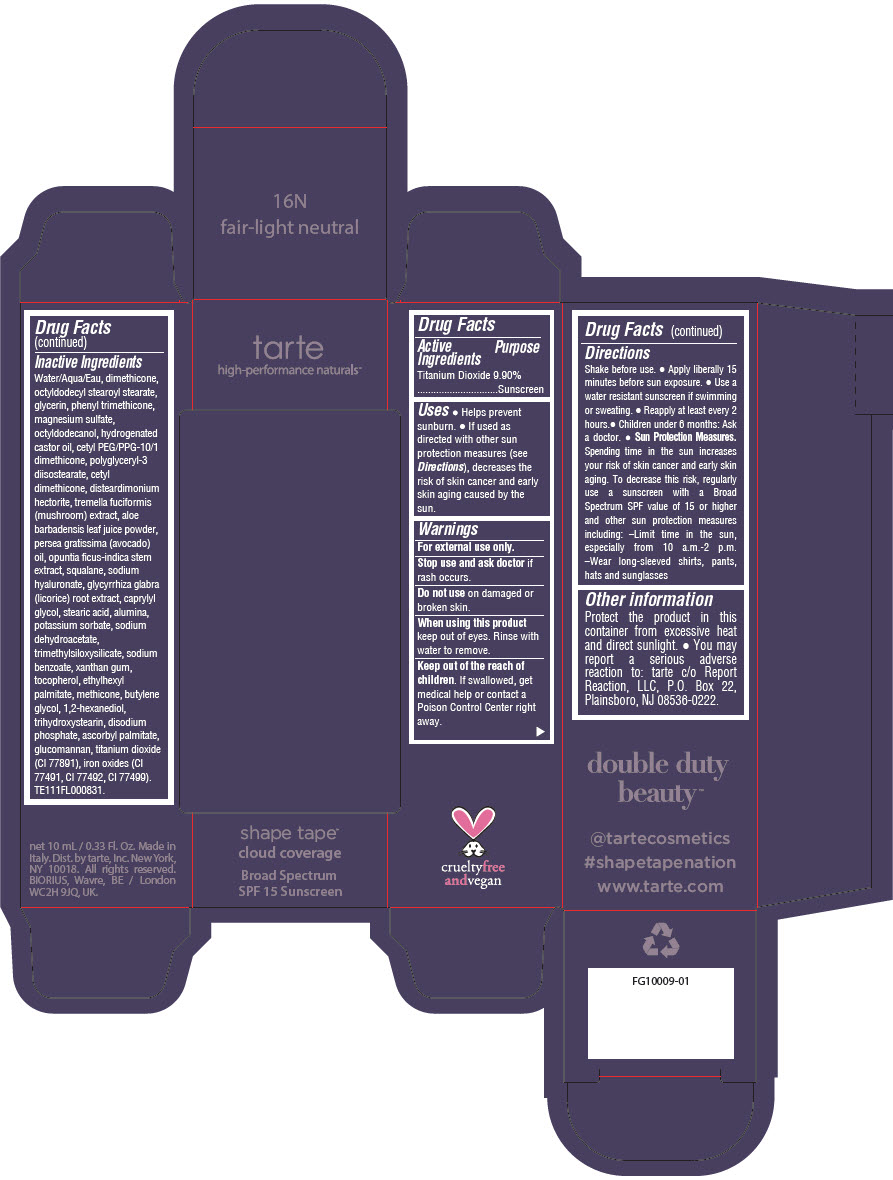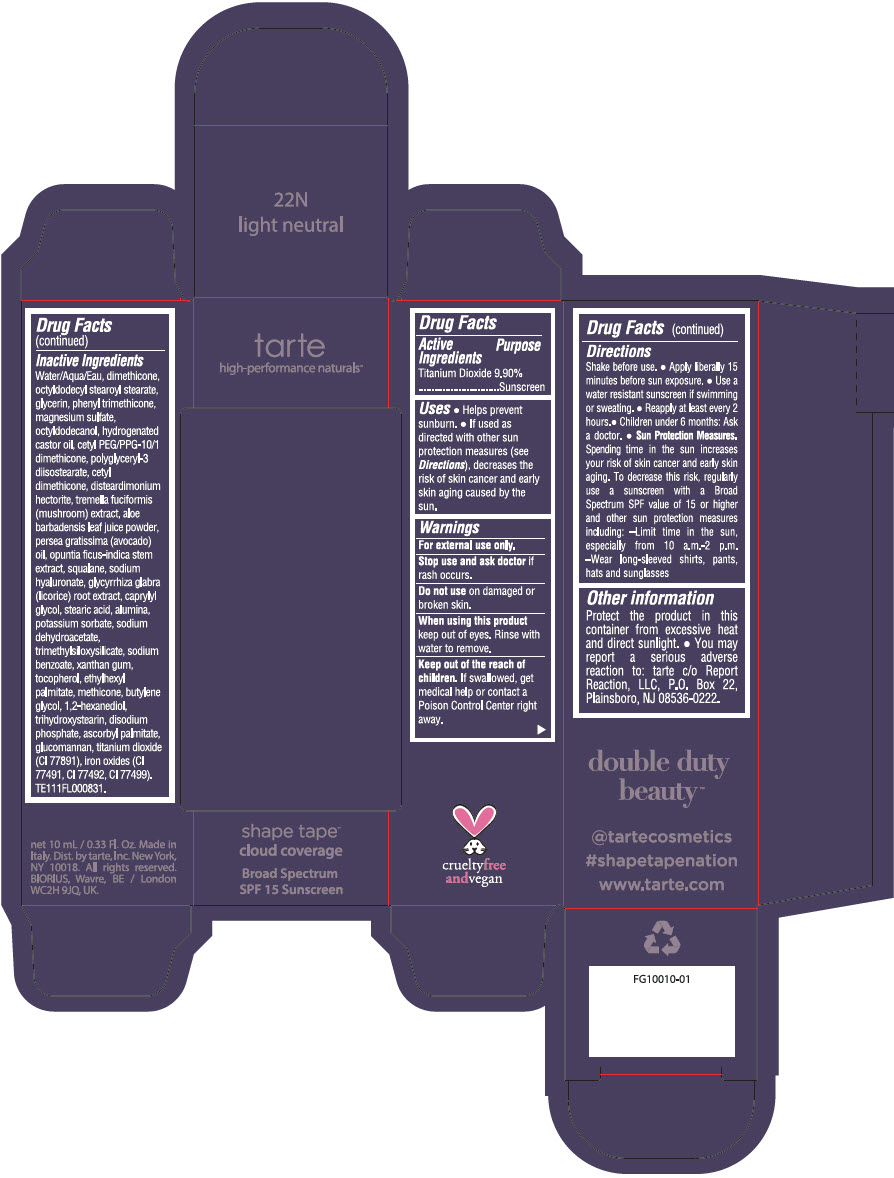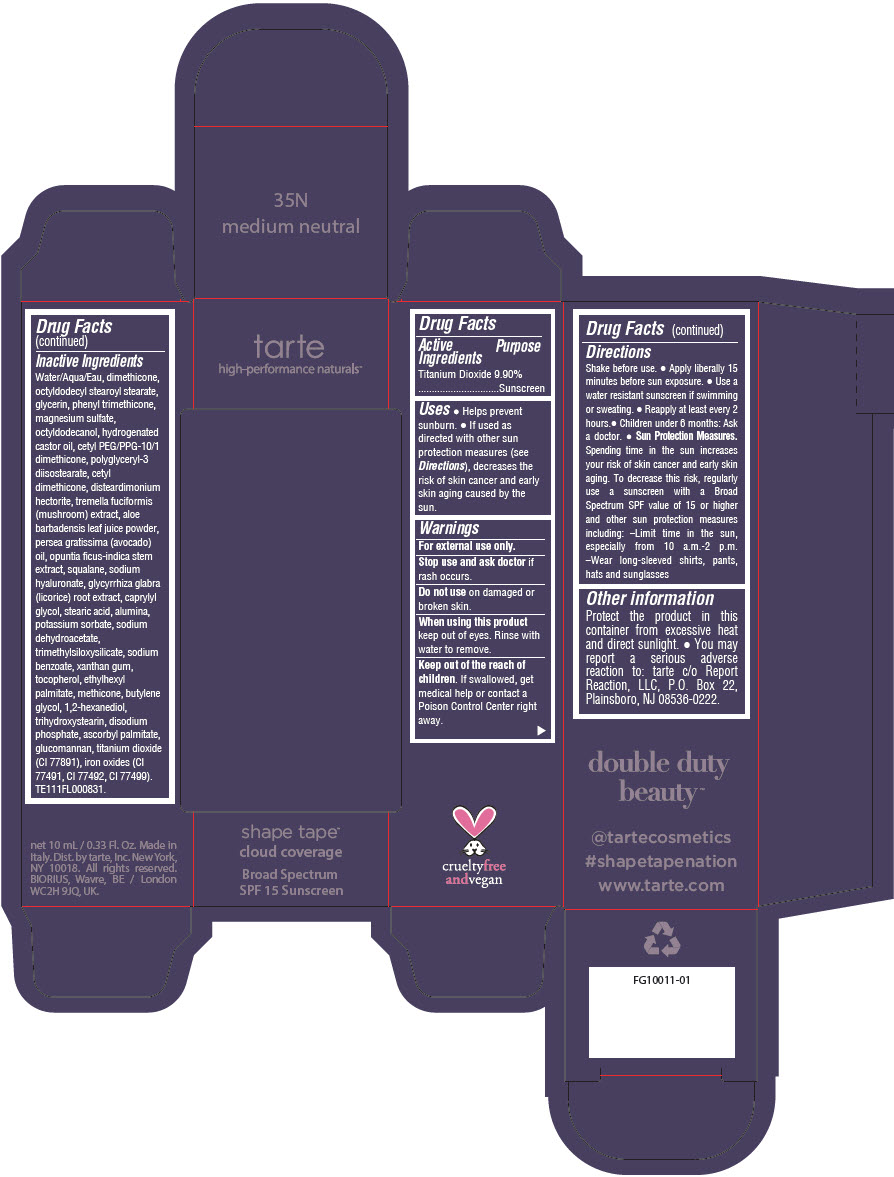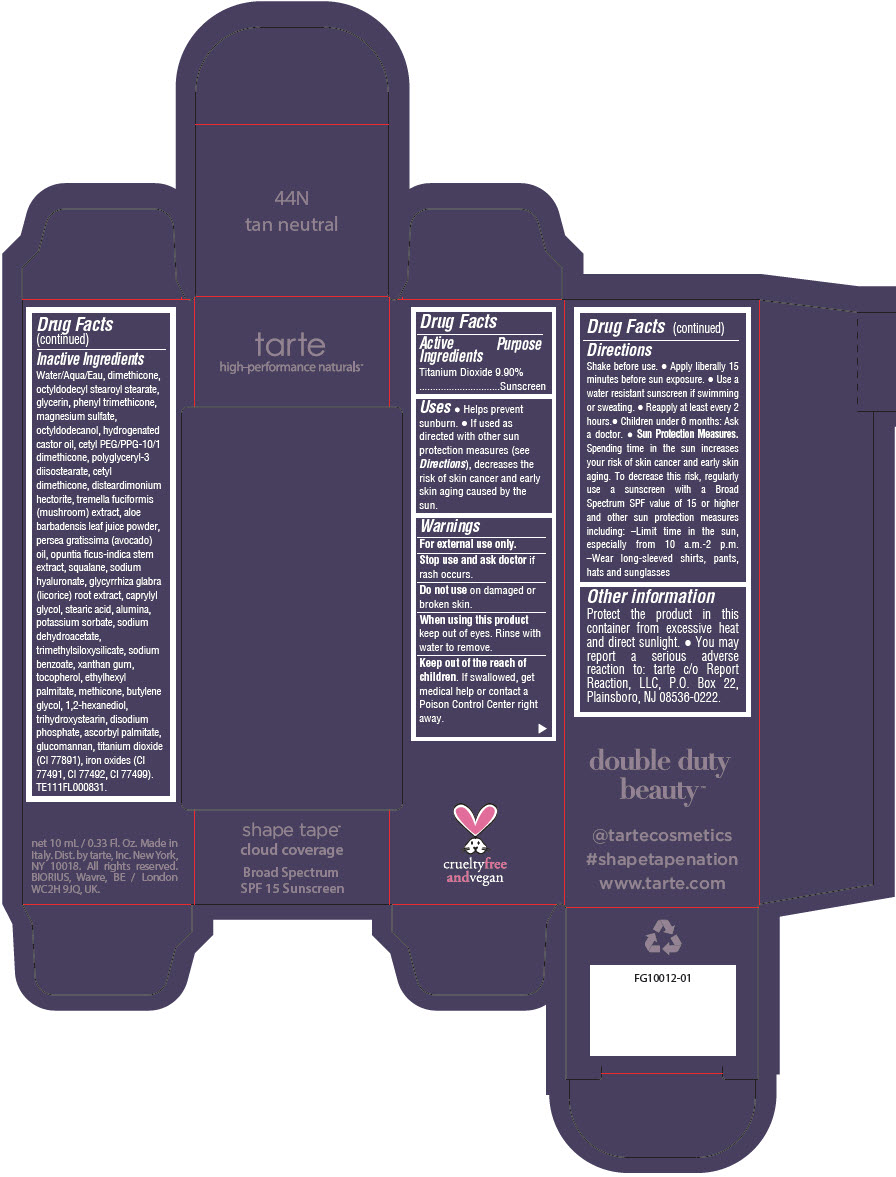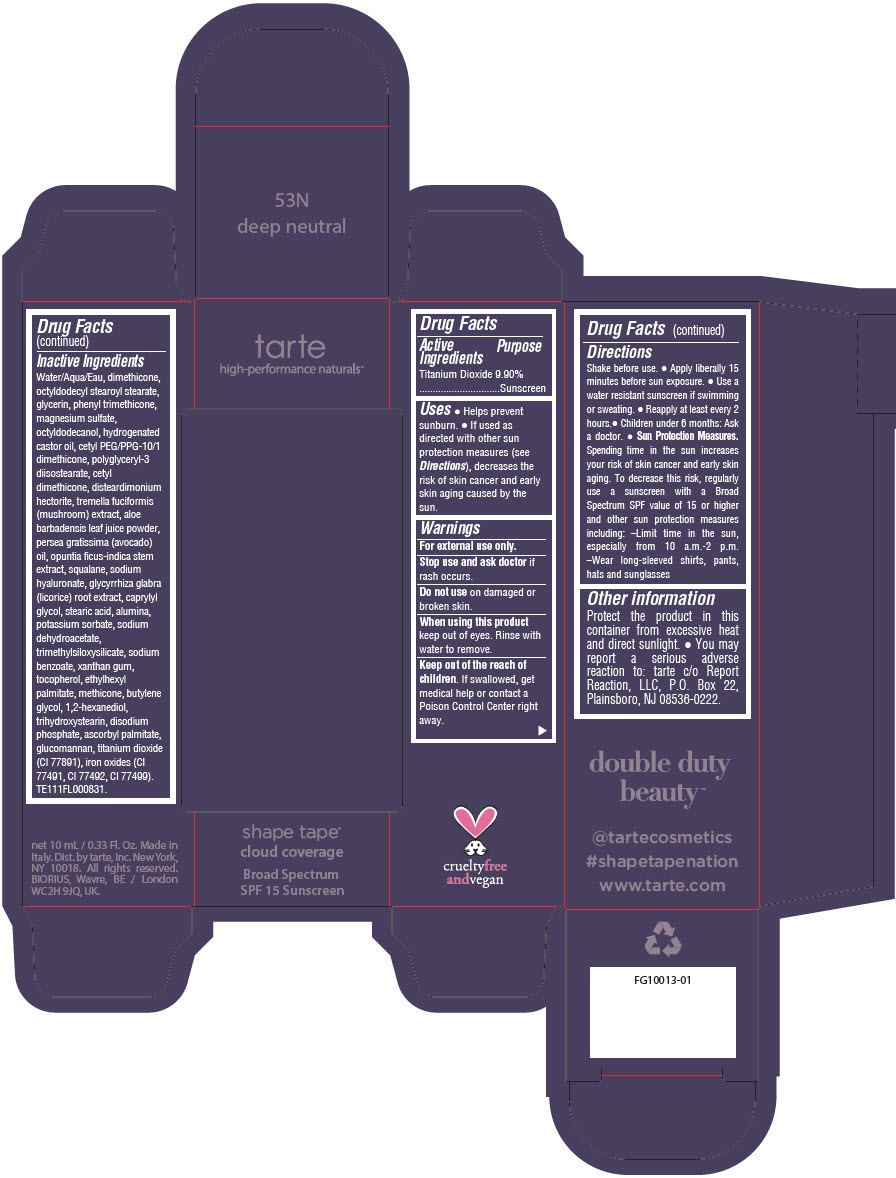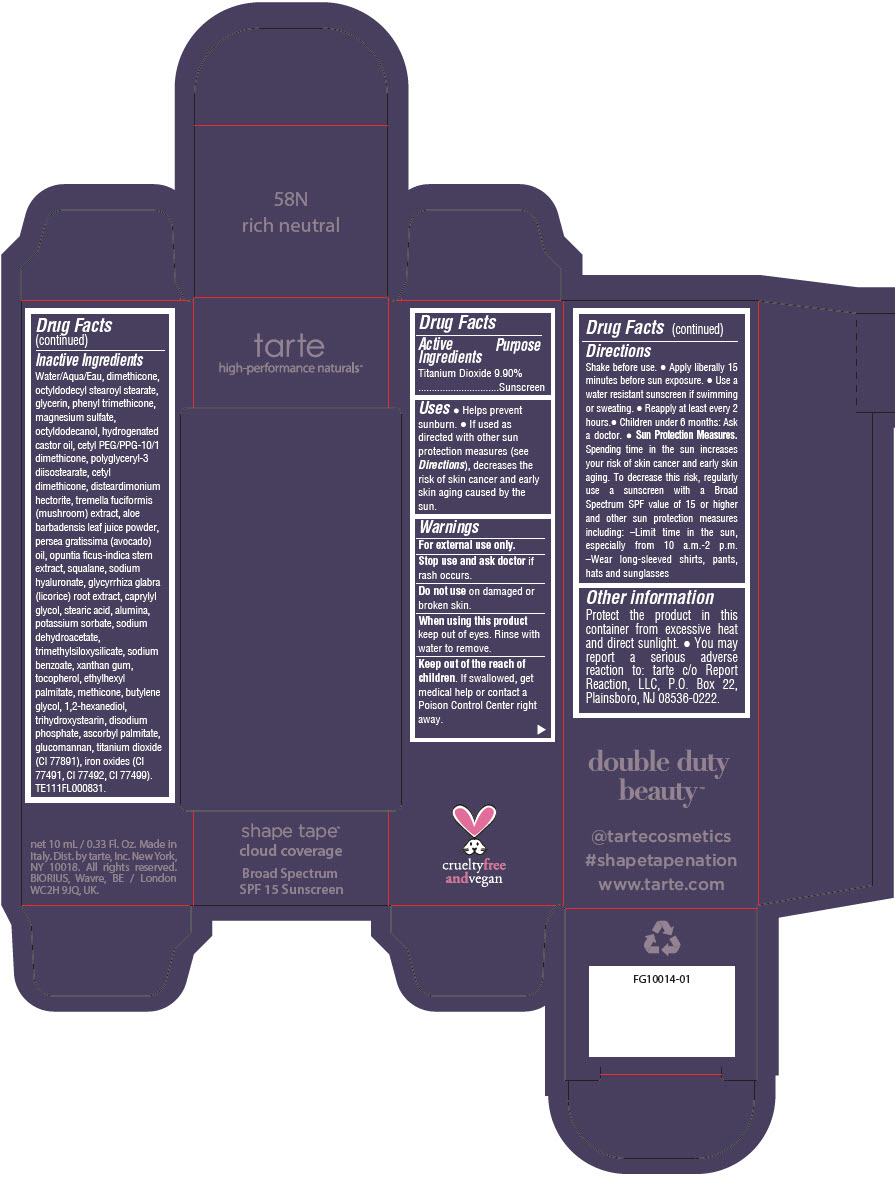 DRUG LABEL: double duty beauty shape tape cloud coverage Broad Spectrum SPF 15 Sunscreen 
NDC: 51060-352 | Form: LIQUID
Manufacturer: Tarte, Inc.
Category: otc | Type: HUMAN OTC DRUG LABEL
Date: 20231221

ACTIVE INGREDIENTS: TITANIUM DIOXIDE 99 mg/1 mL
INACTIVE INGREDIENTS: WATER; DIMETHICONE; OCTYLDODECYL STEAROYL STEARATE; GLYCERIN; PHENYL TRIMETHICONE; MAGNESIUM SULFATE HEPTAHYDRATE; OCTYLDODECANOL; HYDROGENATED CASTOR OIL; CETYL PEG/PPG-10/1 DIMETHICONE (HLB 5); POLYGLYCERYL-3 DIISOSTEARATE; CETYL DIMETHICONE 25; DISTEARDIMONIUM HECTORITE; TREMELLA FUCIFORMIS FRUITING BODY; ALOE VERA LEAF; AVOCADO OIL; SQUALANE; HYALURONATE SODIUM; LICORICE; CAPRYLYL GLYCOL; STEARIC ACID; ALUMINUM OXIDE; POTASSIUM SORBATE; SODIUM DEHYDROACETATE; TRIMETHYLSILOXYSILICATE (M/Q 0.6-0.8); SODIUM BENZOATE; XANTHAN GUM; TOCOPHEROL; ETHYLHEXYL PALMITATE; METHICONE (20 CST); BUTYLENE GLYCOL; 1,2-HEXANEDIOL; TRIHYDROXYSTEARIN; SODIUM PHOSPHATE, DIBASIC, ANHYDROUS; ASCORBYL PALMITATE; KONJAC MANNAN; FERRIC OXIDE RED; FERRIC OXIDE YELLOW; FERROSOFERRIC OXIDE

double duty beauty™ shape tape™ cloud coverage Broad Spectrum SPF 15 Sunscreen

Drug Facts

Active Ingredients

Titanium Dioxide 9.90%

Purpose

Sunscreen

Uses

- Helps prevent sunburn.
- If used as directed with other sun protection measures (see Directions), decreases the risk of skin cancer and early skin aging caused by the sun.

Warnings

For external use only.

Stop use and ask doctor if rash occurs.

Do not use on damaged or broken skin.

When using this product keep out of eyes. Rinse with water to remove.

KEEP OUT OF REACH OF CHILDREN

Keep out of the reach of children. If swallowed, get medical help or contact a Poison Control Center right away.

Directions

- Shake before use.
- Apply liberally 15 minutes before sun exposure.
- Use a water resistant sunscreen if swimming or sweating.
- Reapply at least every 2 hours.
- Children under 6 months: Ask a doctor.
- Sun Protection Measures. Spending time in the sun increases your risk of skin cancer and early skin aging. To decrease this risk, regularly use a sunscreen with a Broad Spectrum SPF value of 15 or higher and other sun protection measures including:
  - Limit time in the sun, especially from 10 a.m.-2 p.m.
  - Wear long-sleeved shirts, pants, hats and sunglasses

Other information

Protect the product in this container from excessive heat and direct sunlight.

- You may report a serious adverse reaction to: tarte c/o Report Reaction, LLC, P.O. Box 22, Plainsboro, NJ 08536-0222.

Inactive Ingredients

Water/Aqua/Eau, dimethicone, octyldodecyl stearoyl stearate, glycerin, phenyl trimethicone, magnesium sulfate, octyldodecanol, hydrogenated castor oil, cetyl PEG/PPG-10/1 dimethicone, polyglyceryl-3 diisostearate, cetyl dimethicone, disteardimonium hectorite, tremella fuciformis (mushroom) extract, aloe barbadensis leaf juice powder, persea gratissima (avocado) oil, opuntia ficus-indica stem extract, squalane, sodium hyaluronate, glycyrrhiza glabra (licorice) root extract, caprylyl glycol, stearic acid, alumina, potassium sorbate, sodium dehydroacetate, trimethylsiloxysilicate, sodium benzoate, xanthan gum, tocopherol, ethylhexyl palmitate, methicone, butylene glycol, 1,2-hexanediol, trihydroxystearin, sodium hyaluronate, disodium phosphate, ascorbyl palmitate, glucomannan, titanium dioxide (CI 77891), iron oxides (CI 77491, CI 77492, CI 77499). TE111FL000831.

Dist. by tarte, Inc. New York,
NY 10018.

PRINCIPAL DISPLAY PANEL - 10 mL Tube Carton - 16N Fair-Light Neutral

tarte
high-performance naturals™

shape tape™
cloud coverage

Broad Spectrum
SPF 15 Sunscreen

PRINCIPAL DISPLAY PANEL - 10 mL Tube Carton - 22N Light Neutral

tarte
high-performance naturals™

shape tape™
cloud coverage

Broad Spectrum
SPF 15 Sunscreen

PRINCIPAL DISPLAY PANEL - 10 mL Tube Carton - 35N Medium Neutral

tarte
high-performance naturals™

shape tape™
cloud coverage

Broad Spectrum
SPF 15 Sunscreen

PRINCIPAL DISPLAY PANEL - 10 mL Tube Carton - 44N Tan Neutral

tarte
high-performance naturals™

shape tape™
cloud coverage

Broad Spectrum
SPF 15 Sunscreen

PRINCIPAL DISPLAY PANEL - 10 mL Tube Carton - 53N Deep Neutral

tarte
high-performance naturals™

shape tape™
cloud coverage

Broad Spectrum
SPF 15 Sunscreen

PRINCIPAL DISPLAY PANEL - 10 mL Tube Carton - 58N Rich Neutral

tarte
high-performance naturals™

shape tape™
cloud coverage

Broad Spectrum
SPF 15 Sunscreen